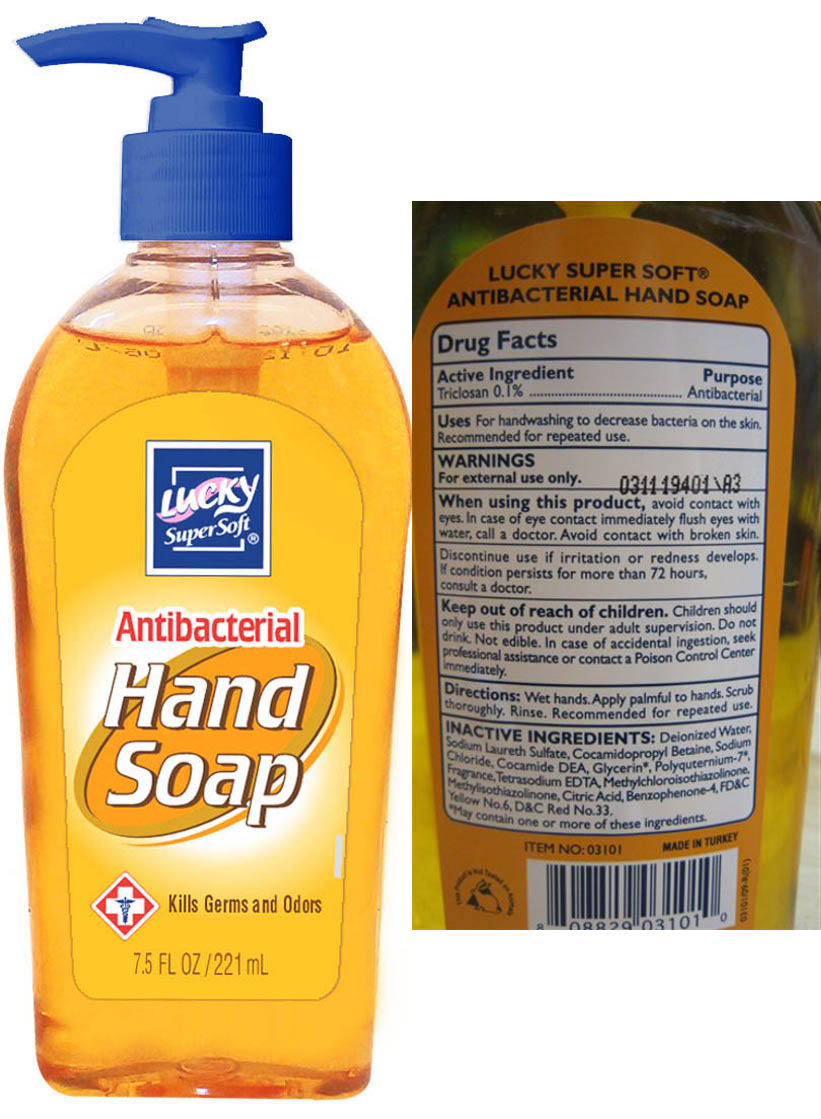 DRUG LABEL: Antibacterial Hand Soap
NDC: 20276-165 | Form: LIQUID
Manufacturer: Delta Brands Inc
Category: otc | Type: HUMAN OTC DRUG LABEL
Date: 20110920

ACTIVE INGREDIENTS: TRICLOSAN 0.1 mL/100 mL
INACTIVE INGREDIENTS: WATER; SODIUM LAURETH SULFATE; COCAMIDOPROPYL BETAINE; SODIUM CHLORIDE; COCO DIETHANOLAMIDE; GLYCERIN; EDETATE SODIUM; METHYLCHLOROISOTHIAZOLINONE; METHYLISOTHIAZOLINONE; CITRIC ACID MONOHYDRATE; FD&C YELLOW NO. 6; D&C RED NO. 33

Drug Facts

Active Ingredient

Triclosan 0.1%

Purpose

Antibacterial

Uses

For handwashing to decrease bacteria on the skin. Recommended for repeated use.

Warnings

For external use only

When using this product

avoid contact with eyes. In case of eye contact immediately flush eyes with water, call a doctor. Avoid contact with broken skin.
Discontinue use if irritation or redness develops. If condition persists for more than 72 hours, consult a doctor.

Keep out of reach of children

Children should only use this product with adult supervision. Do not drink. Not edible. In case of accidental ingestion seek professional assistance or contact Poison Control Center immediately.

Directions

Wet hands. Apply palmful to hands. Scrub thoroughly. Rinse. Recommended for repeated use

INACTIVE INGREDIENT

Deionized Water, Sodium Laureth Sulfate, Cocamidopropyl Betaine,Sodium Chloride, Cocamide DEA, Glycerin*, Polyquaternium-7*, Fragrance, Tetrasodium EDTA, Methylchloroisothiazolinone, Methylisothiazolinone, Citric Acid, Benzophenone-4, FDC Yellow No. 6, DC Red No 33
*May contain one or more of these ingredients

Product Label